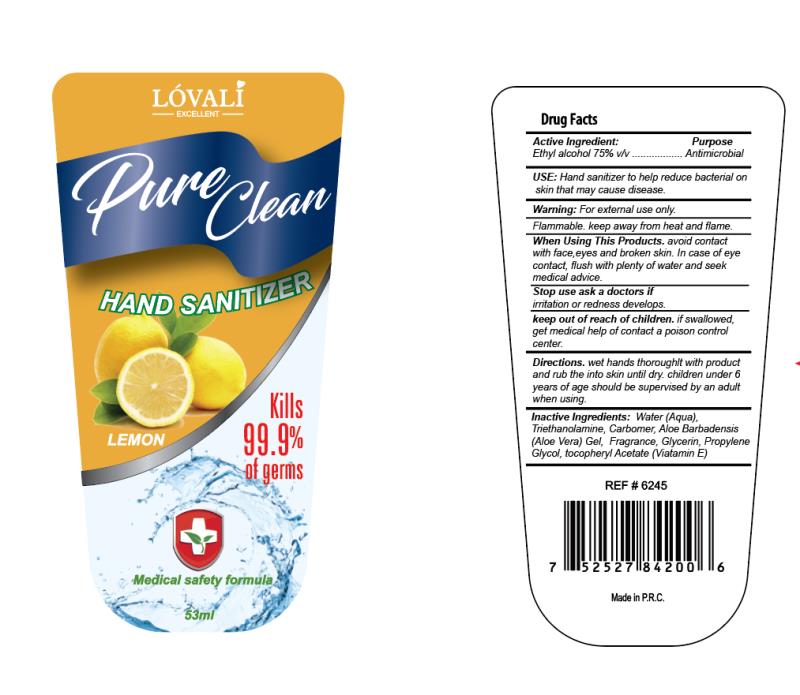 DRUG LABEL: pure clean hand sanitizer
NDC: 54304-001 | Form: GEL
Manufacturer: Zhejiang Meizhiyuan Cosmetics Co.,Ltd
Category: otc | Type: HUMAN OTC DRUG LABEL
Date: 20200325

ACTIVE INGREDIENTS: ALCOHOL 39.75 mL/53 mL
INACTIVE INGREDIENTS: GLYCERIN; WATER; PROPYLENE GLYCOL; TROLAMINE; .ALPHA.-TOCOPHEROL; ALOE VERA LEAF; CARBOMER HOMOPOLYMER, UNSPECIFIED TYPE

DOSAGE AND ADMINISTRATION

Flammable. keep away from heat and flame.

WARNINGS

For extermal use only.

keep out of reach of children

INDICATIONS AND USAGE

When Using This Products. avoid contact with face,eyes and broken skin.

In case of eye contact, flush with plenty of water and seek medical advice.

ACTIVE INGREDIENT

Ethyl alcohol 75%

INACTIVE INGREDIENT

Inactive Ingredients: Water (Aqua). Triethanolamine, Carbormer, Aloe Barbadensis(Aloe Vera) Gel, Fragrance, Gilycerin, Propylene
Glycol, tocopherylAcetate (Miatamin E).

PURPOSE

Disinfection
Sterilization
No Rinseing

Antimicrobial